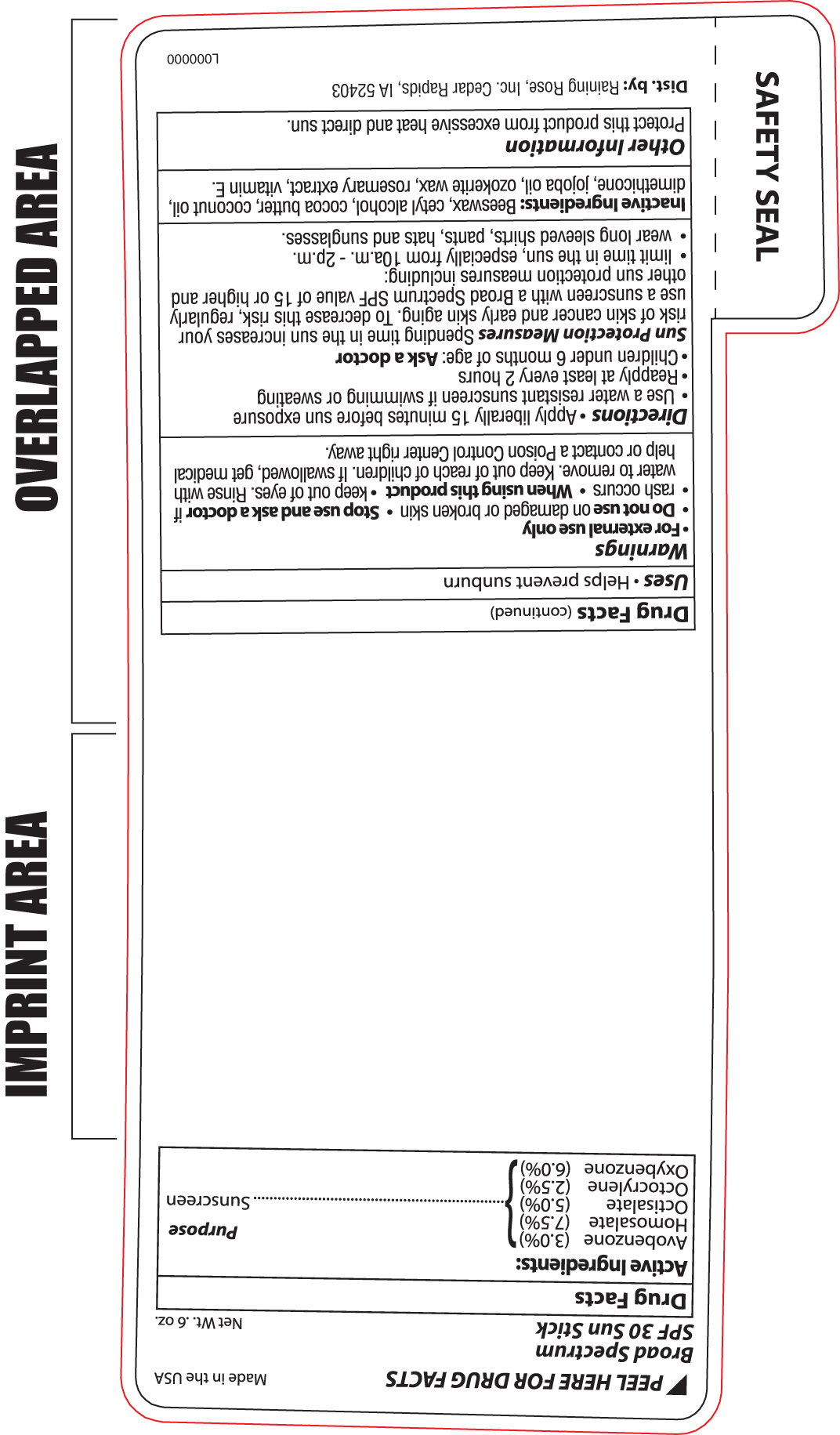 DRUG LABEL: RR SPF30 Sun Stick
NDC: 58418-276 | Form: STICK
Manufacturer: Tropical Enterprises International, Inc
Category: otc | Type: HUMAN OTC DRUG LABEL
Date: 20200202

ACTIVE INGREDIENTS: OCTISALATE 5 mg/1 mL; OCTOCRYLENE 2.5 mg/1 mL; OXYBENZONE 6 mg/1 mL; HOMOSALATE 7.5 mg/1 mL; AVOBENZONE 3 mg/1 mL
INACTIVE INGREDIENTS: YELLOW WAX; .ALPHA.-TOCOPHEROL ACETATE; COCOA BUTTER; DIMETHICONE CROSSPOLYMER (450000 MPA.S AT 12% IN CYCLOPENTASILOXANE); JOJOBA OIL; CETYL ALCOHOL; COCONUT OIL; CERESIN; ROSEMARY

Raining_Broad Spectrum Spf30 Sunstick 276

ACTIVE INGREDIENT

Avobenzone 3%

Homosalate 7.5%

Octisalate 5%

Octocrylene 2.5%

Oxybenzone 6%

INSTRUCTIONS FOR USE

Uses - Helps prevent sunburn

WARNINGS

- For external use only
- Do not use on damaged or broken skin
- Stop use and ask a doctor if rash occurs
- When using this product keep out of eyes. Rinse with water to remove.
- Keep out of reach of children. If swallowed, get medical help or contact a Poison Control Center right away.

Directions:

Apply liberally 15 minutes before sun exposure

- Use a water resistant sunscreen if swimming or sweating
- Reapply at least every 2 hours
- children under 6 months of age: Ask a Doctor

Sun Protection Measures: Spending time in the sun increases your risk of skin cancer and early skin aging. To decrease this risk, regularly use a sunscreen with a Broad Spectrum SPF value of 15 or higher and other sun protection measures including:

- limit time in the sun, especially from 10am - 2pm.
- wear long sleeved shirts, pants, hats and sunglasses

INACTIVE INGREDIENT

Beeswax, cetyl alcohol, cocoa butter, coconut oil, dimethicone, jojoba oil, ozokerite wax, rosemary extract, vitamin E

Other Information:

Protect this product from excessive heat and direct sun.